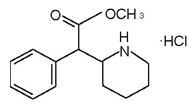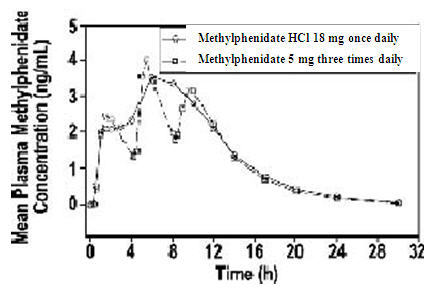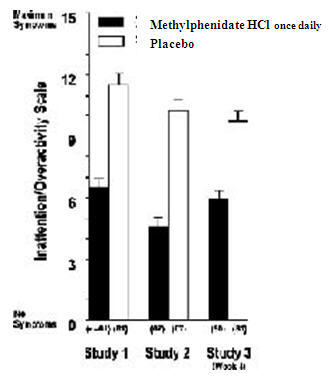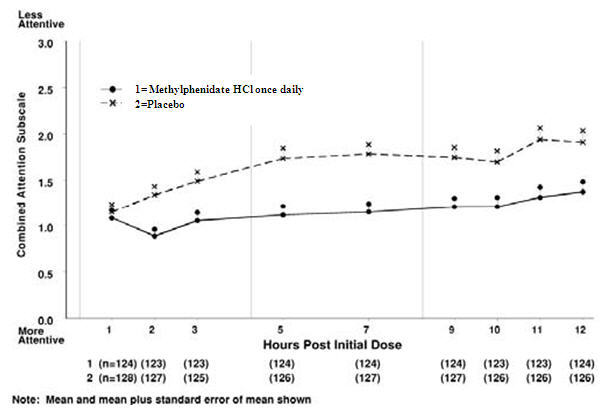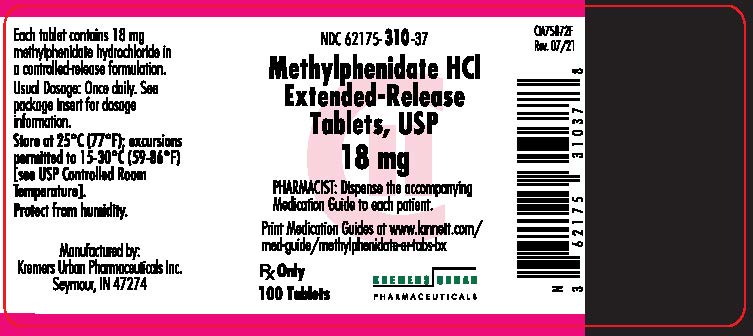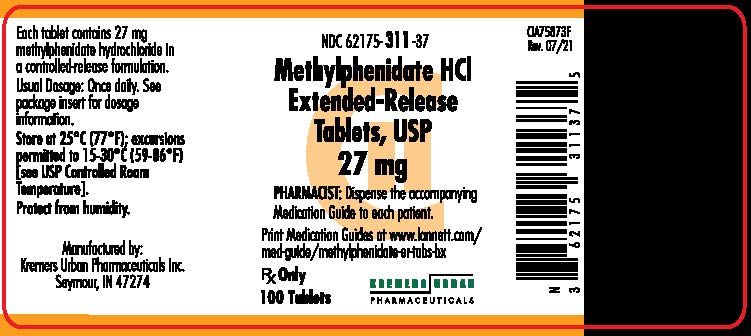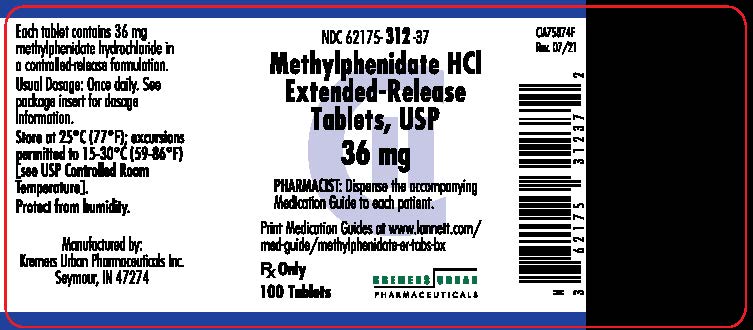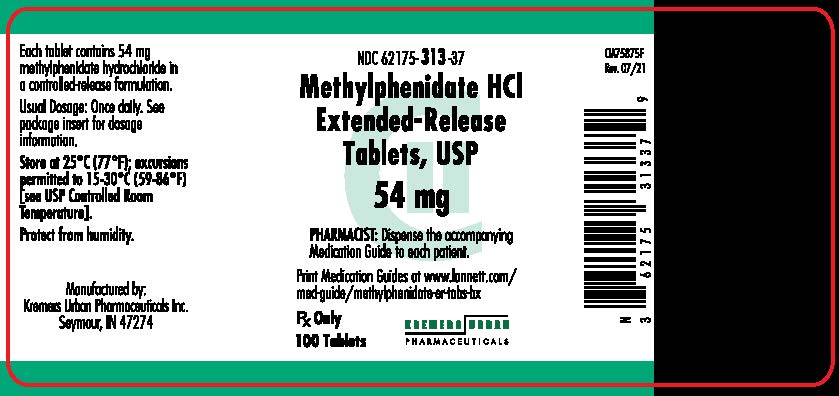 DRUG LABEL: Methylphenidate Hydrochloride
NDC: 62175-310 | Form: TABLET, EXTENDED RELEASE
Manufacturer: Lannett Company, Inc.
Category: prescription | Type: HUMAN PRESCRIPTION DRUG LABEL
Date: 20260106
DEA Schedule: CII

ACTIVE INGREDIENTS: METHYLPHENIDATE HYDROCHLORIDE 18 mg/1 1
INACTIVE INGREDIENTS: CARBOXYMETHYLCELLULOSE SODIUM (0.7 CARBOXYMETHYL SUBSTITUTION PER SACCHARIDE; 400 MPA.S AT 1%); SILICON DIOXIDE; STARCH, CORN; ETHYLCELLULOSE (10 MPA.S); HYDROXYPROPYL CELLULOSE (1600000 WAMW); HYPROMELLOSES; HYPROMELLOSE ACETATE SUCCINATE 06081224 (3 MM2/S); MAGNESIUM STEARATE; CELLULOSE, MICROCRYSTALLINE; POLYETHYLENE GLYCOL 3350; SUCROSE; TALC; TITANIUM DIOXIDE; TRIETHYL CITRATE; FERRIC OXIDE RED

HIGHLIGHTS OF PRESCRIBING INFORMATION

These highlights do not include all the information needed to use METHYLPHENIDATE HCl EXTENDED-RELEASE TABLETS safely and effectively. See full prescribing information for METHYLPHENIDATE HCl EXTENDED-RELEASE TABLETS.
METHYLPHENIDATE hydrochloride extended-release tablets, USP for oral use
CII
Initial U.S. Approval: 2000

RECENT MAJOR CHANGES

Indications and Usage (1) | 09/2025
Warnings and Precautions (5.8) | 09/2025

WARNING: ABUSE, MISUSE, AND ADDICTION

See full prescribing information for complete boxed warning.

Methylphenidate HCl Extended-Release Tablets has a high potential for abuse and misuse, which can lead to the development of a substance use disorder, including addiction. Misuse and abuse of CNS stimulants, including Methylphenidate HCl Extended-Release Tablets, can result in overdose and death (5.1, 9.2, 10):

• Before prescribing Methylphenidate HCl Extended-Release Tablets, assess each patient’s risk for abuse, misuse, and addiction.

• Educate patients and their families about these risks, proper storage of the drug, and proper disposal of any unused drug.

• Throughout treatment, reassess each patient’s risk and frequently monitor for signs and symptoms of abuse, misuse, and addiction.

1 INDICATIONS AND USAGE

Methylphenidate HCl Extended-Release Tablets is a CNS stimulant indicated for the treatment of Attention Deficit Hyperactivity Disorder (ADHD) in children 6 years of age and older, adolescents, and adults up to the age of 65. (1)

Limitations of Use

The use of Methylphenidate HCl Extended-Release Tablets is not recommended in pediatric patients younger than 6 years of age because they had higher plasma exposure and a higher incidence of adverse reactions (e.g., weight loss) than patients 6 years and older at the same dosage (5.8, 8.4).

2 DOSAGE AND ADMINISTRATION

- Methylphenidate HCl Extended-Release Tablets should be taken once daily in the morning and swallowed whole with the aid of liquids. Methylphenidate HCl Extended-Release Tablets should not be chewed or crushed. Methylphenidate HCl Extended-Release Tablets may be taken with or without food. (2.2)
- For children and adolescents new to methylphenidate, the recommended starting dosage is 18 mg once daily. Dosage may be increased by 18 mg/day at weekly intervals and should not exceed 54 mg/day in children and 72 mg/day in adolescents. (2.3)
- For adult patients new to methylphenidate, the recommended starting dose is 18 or 36 mg/day. Dosage may be increased by 18 mg/day at weekly intervals and should not exceed 72 mg/day for adults. (2.3)
- For patients currently using methylphenidate, dosing is based on current dose regimen and clinical judgment. (2.4)

3 DOSAGE FORMS AND STRENGTHS

Tablets: 18, 27, 36, and 54 mg (3)

4 CONTRAINDICATIONS

- Known hypersensitivity to the product (4.1)
- Do not use Methylphenidate HCl Extended-Release Tablets in patients currently using or within 2 weeks of using an MAO inhibitor (4.2)

5 WARNINGS AND PRECAUTIONS

- Risks to Patients with Serious Cardiac Disease: Avoid in patients with known structural cardiac abnormalities, cardiomyopathy, serious cardiac arrhythmias, coronary artery disease, or other serious cardiac disease. (5.2)
- Increase in Blood Pressure and Heart Rate: Monitor blood pressure and pulse. (5.3)
- Psychiatric Adverse Reactions: Prior to initiating Methylphenidate HCl Extended-Release Tablets, screen patients for risk factors for developing a manic episode. If new psychotic or manic symptoms occur, consider discontinuing Methylphenidate HCl Extended-Release Tablets. (5.4)
- Seizures: Stimulants may lower the convulsive threshold. Discontinue in the presence of seizures. (5.5)
- Priapism: If abnormally sustained or frequent and painful erections occur, patients should seek immediate medical attention. (5.6)
- Peripheral Vasculopathy, including Raynaud’s Phenomenon: Careful observation for digital changes is necessary during Methylphenidate HCl Extended-Release Tablets treatment. Further clinical evaluation (e.g., rheumatology referral) may be appropriate for patients who develop signs or symptoms of peripheral vasculopathy. (5.7)
- Long-Term Suppression of Growth in Pediatric Patients: Closely monitor growth (height and weight) in pediatric patients. Pediatric patients not growing or gaining height or weight as expected may need to have their treatment interrupted. (5.8)
- Gastrointestinal obstruction with preexisting GI narrowing. (5.9)
- Hematologic monitoring: Periodic CBC, differential, and platelet counts are advised during prolonged therapy. (5.10)
- Acute Angle Closure Glaucoma: Methylphenidate HCl Extended-Release Tablets -treated patients considered at risk for acute angle closure glaucoma (e.g., patients with significant hyperopia) should be evaluated by an ophthalmologist. (5.11)
- Increased Intraocular Pressure and Glaucoma: Prescribe Methylphenidate HCl Extended-Release Tablets to patients with open-angle glaucoma or abnormally increased IOP only if the benefit of treatment is considered to outweigh the risk. Closely monitor patients with a history of increased IOP or open angle glaucoma. (5.12)
- Motor and Verbal Tics, and Worsening of Tourette’s Syndrome: Before initiating Methylphenidate HCl Extended-Release Tablets, assess the family history and clinically evaluate patients for tics or Tourette’s syndrome. Regularly monitor patients for the emergence or worsening of tics or Tourette’s syndrome. Discontinue treatment if clinically appropriate. (5.13)

6 ADVERSE REACTIONS

The most common adverse reaction in double-blind clinical trials (>5%) in children and adolescents was abdominal pain upper. The most common adverse reactions in double-blind clinical trials (>5%) in adult patients were decreased appetite, headache, dry mouth, nausea, insomnia, anxiety, dizziness, weight decreased, irritability, and hyperhidrosis. (6.1 and 6.2)

The most common adverse reactions associated with discontinuation (≥1%) from either pediatric or adult clinical trials were anxiety, irritability, insomnia, and blood pressure increased. (6.3)

To report SUSPECTED ADVERSE REACTIONS, contact Kremers Urban Pharmaceuticals Inc. at 1-844-834-0530 or FDA at 1-800-FDA-1088 or www.fda.gov/medwatch.

7 DRUG INTERACTIONS

- Methylphenidate HCl Extended-Release Tablets may increase blood pressure; use cautiously with vasopressors (7.2)
- Inhibition of metabolism of coumarin anticoagulants, anticonvulsants, and some antidepressants (7.3)

8 USE IN SPECIFIC POPULATIONS

- Caution should be exercised if administered to nursing mothers (8.3)
- Safety and efficacy has not been established in children less than six years old or elderly patients greater than 65 years of age (8.4 and 8.5)

FULL PRESCRIBING INFORMATION

RECENT MAJOR CHANGES

Boxed Warning 10/2023

Indications and Usage (1) 10/2023

Dosage and Administration (2.1, 2.6) 10/2023

Dosage and Administration, Maintenance/Extended Treatment (2.5)

Removed 10/2023

Contraindications (4) 10/2023

Warnings and Precautions (5.1, 5.2,5.3, 5.4, 5.6, 5.7, 5.8, 5.11, 5.12, 5.13)

10/2023

Warnings and Precautions (5.7) Removed 10/2023

WARNING: ABUSE, MISUSE, AND ADDICTION

Methylphenidate HCl Extended-Release Tablets have a high potential for abuse and misuse, which can lead to the development of a substance use disorder, including addiction. Misuse and abuse of CNS stimulants, including Methylphenidate HCl Extended-Release Tablets, can result in overdose and death [see Overdosage (10)], and this risk is increased with higher doses or unapproved methods of administration, such as snorting or injection.

Before prescribing Methylphenidate HCl Extended-Release Tablets, assess each patient’s risk for abuse, misuse, and addiction. Educate patients and their families about these risks, proper storage of the drug, and proper disposal of any unused drug. Throughout Methylphenidate HCl Extended-Release Tablets treatment, reassess each patient’s risk of abuse, misuse, and addiction and frequently monitor for signs and symptoms of abuse, misuse, and addiction [see Warnings and Precautions (5.1) and Drug Abuse and Dependence (9.2)].

1 INDICATIONS AND USAGE

Methylphenidate HCl Extended-Release Tablets are indicated for the treatment of Attention Deficit Hyperactivity Disorder (ADHD) in children 6 years of age and older, adolescents, and adults up to the age of 65 [see Clinical Studies (14)].

Limitations of Use

The use of Methylphenidate HCl Extended-Release Tablets is not recommended in pediatric patients younger than 6 years of age because they had higher plasma exposure and a higher incidence of adverse reactions (e.g., weight loss) than patients 6 years and older at the same dosage [see Warnings and Precautions (5.8), Use in Specific Populations (8.4)].

2 DOSAGE AND ADMINISTRATION

2.1 Pretreatment Screening

Prior to treating patients with Methylphenidate HCl Extended-Release Tablets, assess:

- for the presence of cardiac disease (i.e., perform a careful history, family history of sudden death or ventricular arrhythmia, and physical exam) [see Warnings and Precautions (5.2)].
- the family history and clinically evaluate patients for motor or verbal tics or Tourette’s syndrome before initiating Methylphenidate HCl Extended-Release Tablets [see Warnings and Precautions (5.13)].

2.2 Recommended Dosage

Methylphenidate HCl Extended-Release Tablets should be administered orally once daily in the morning with or without food.

Methylphenidate HCl Extended-Release Tablets must be swallowed whole with the aid of liquids, and must not be chewed, divided, or crushed [see Patient Counseling Information (17)].

2.3 Patients New to Methylphenidate

The recommended starting dose of Methylphenidate HCl Extended-Release Tablets for patients who are not currently taking methylphenidate or stimulants other than methylphenidate is 18 mg once daily for children and adolescents and 18 or 36 mg once daily for adults (see Table 1).

Table 1. Methylphenidate HCl Extended-Release Tablets Recommended Starting Doses and Dose Ranges

Patient Age | Recommended Starting Dose | Dose Range
Children 6-12 years of age | 18 mg/day | 18 mg - 54 mg/day
Adolescents 13-17 years of age | 18 mg/day | 18 mg - 72 mg/day; not to exceed 2 mg/kg/day
Adults 18-65 years of age | 18 or 36 mg/day | 18 mg - 72 mg/day

2.4 Patients Currently Using Methylphenidate

The recommended dose of Methylphenidate HCl Extended-Release Tablets for patients who are currently taking methylphenidate twice daily or three times daily at doses of 10 to 60 mg/day is provided in Table 2. Dosing recommendations are based on current dose regimen and clinical judgment. Conversion dosage should not exceed 72 mg daily.

Table 2. Recommended Dose Conversion from Methylphenidate Regimens to Methylphenidate HCl Extended-Release Tablets

Previous Methylphenidate Daily Dose | Recommended Methylphenidate HCl Extended-Release Tablets Starting Dose
5 mg Methylphenidate twice daily or three times daily | 18 mg every morning
10 mg Methylphenidate twice daily or three times daily | 36 mg every morning
15 mg Methylphenidate twice daily or three times daily | 54 mg every morning
20 mg Methylphenidate twice daily or three times daily | 72 mg every morning

Other methylphenidate regimens: Clinical judgment should be used when selecting the starting dose.

2.5 Dose Titration

Doses may be increased in 18 mg increments at weekly intervals for patients who have not achieved an optimal response at a lower dose. Daily dosages above 54 mg in children and 72 mg in adolescents have not been studied and are not recommended. Daily dosages above 72 mg in adults are not recommended.

A 27 mg dosage strength is available for physicians who wish to prescribe between the 18 mg and 36 mg dosages.

2.6 Dosage Reduction and Discontinuation

If paradoxical aggravation of symptoms or other adverse reactions occur, reduce dosage or, if necessary, discontinue Methylphenidate HCl Extended-Release Tablets.

If improvement is not observed after appropriate dosage adjustment over a one-month period, discontinue Methylphenidate HCl Extended-Release Tablets.

3 DOSAGE FORMS AND STRENGTHS

Methylphenidate HCl Extended-Release Tablets, USP are available in the following dosage strengths: 18 mg tablets are pink and imprinted with “18”, 27 mg tablets are yellow and imprinted with “27”, 36 mg tablets are pink and imprinted with “36”, and 54 mg tablets are pink and imprinted with “54”.

4 CONTRAINDICATIONS

4.1 Hypersensitivity to Methylphenidate

Hypersensitivity reactions, such as angioedema and anaphylactic reactions, have been observed in patients treated with Methylphenidate HCl Extended-Release Tablets. Therefore, Methylphenidate HCl Extended-Release Tablets are contraindicated in patients known to be hypersensitive to methylphenidate or other components of the product [see Adverse Reactions (6.5)].

4.2 Monoamine Oxidase Inhibitors

Methylphenidate HCl Extended-Release Tablets are contraindicated during treatment with monoamine oxidase (MAO) inhibitors, and also within a minimum of 14 days following discontinuation of a MAO inhibitor (hypertensive crises may result) [see Drug Interactions (7.1)].

5 WARNINGS AND PRECAUTIONS

5.1 Abuse, Misuse, and Addiction

Methylphenidate HCl Extended-Release Tablets have a high potential for abuse and misuse. The use of Methylphenidate HCl Extended-Release Tablets expose individuals to the risks of abuse and misuse, which can lead to the development of a substance use disorder, including addiction. Methylphenidate HCl Extended-Release Tablets can be diverted for non-medical use into illicit channels or distribution [see Drug Abuse and Dependence (9.2)]. Misuse and abuse of CNS stimulants, including Methylphenidate HCl Extended-Release Tablets, can result in overdose and death [see Overdosage (10)], and this risk is increased with higher doses or unapproved methods of administration, such as snorting or injection.

Before prescribing Methylphenidate HCl Extended-Release Tablets, assess each patient’s risk for abuse, misuse, and addiction. Educate patients and their families about these risks and proper disposal of any unused drug. Advise patients to store Methylphenidate HCl Extended-Release Tablets in a safe place, preferably locked, and instruct patients to not give Methylphenidate HCl Extended-Release Tablets to anyone else. Throughout Methylphenidate HCl Extended-Release Tablets treatment, reassess each patient’s risk of abuse, misuse, and addiction and frequently monitor for signs and symptoms of abuse, misuse, and addiction.

5.2 Risks to Patients with Serious Cardiac Disease

Sudden death has been reported in patients with structural cardiac abnormalities or other serious cardiac disease who were treated with CNS stimulants at the recommended ADHD dosage.

Avoid Methylphenidate HCl Extended-Release Tablets use in patients with known structural cardiac abnormalities, cardiomyopathy, serious cardiac arrhythmia, coronary artery disease, or other serious cardiac disease.

5.3 Increased Blood Pressure and Heart Rate

CNS stimulants may cause an increase in blood pressure (mean increase approximately 2 to 4 mmHg) and heart rate (mean increase approximately 3 to 6 bpm). Some patients may have larger increases.

Monitor all Methylphenidate HCl Extended-Release Tablets-treated patients for hypertension and tachycardia.

5.4 Psychiatric Adverse Reactions

Exacerbation of Pre-existing Psychosis

CNS stimulants may exacerbate symptoms of behavior disturbance and thought disorder in patients with a pre-existing psychotic disorder.

Induction of a Manic Episode in Patients with Bipolar Disorder

CNS stimulants may induce a manic or mixed episode in patients. Prior to initiating Methylphenidate HCl Extended-Release Tablets treatment, screen patients for risk factors for developing a manic episode (e.g., comorbid or history of depressive symptoms or a family history of suicide, bipolar disorder, or depression).

New Psychotic or Manic Symptoms

CNS stimulants, at the recommended dosage, may cause psychotic or manic symptoms (e.g., hallucinations, delusional thinking, or mania) in patients without a prior history of psychotic illness or mania. In a pooled analysis of multiple short-term, placebo-controlled studies of CNS stimulants, psychotic or manic symptoms occurred in approximately 0.1% of CNS stimulant-treated patients, compared with 0% of placebo-treated patients. If such symptoms occur, consider discontinuing Methylphenidate HCl Extended-Release Tablets.

5.5 Seizures

There is some clinical evidence that stimulants may lower the convulsive threshold in patients with prior history of seizures, in patients with prior EEG abnormalities in absence of seizures, and, very rarely, in patients without a history of seizures and no prior EEG evidence of seizures. In the presence of seizures, the drug should be discontinued.

5.6 Priapism

Prolonged and painful erections, sometimes requiring surgical intervention, have been reported with methylphenidate use in both adult and pediatric male patients [see Adverse Reactions (6.5)]. Although priapism was not reported with methylphenidate initiation, it developed after some time on methylphenidate, often subsequent to an increase in dosage. Priapism also occurred during methylphenidate withdrawal (drug holidays or during discontinuation).

Methylphenidate HCl Extended-Release Tablets-treated patients who develop abnormally sustained or frequent and painful erections should seek immediate medical attention.

5.7 Peripheral Vasculopathy, including Raynaud’s Phenomenon

CNS stimulants, including Methylphenidate HCl Extended-Release Tablets, used to treat ADHD are associated with peripheral vasculopathy, including Raynaud’s phenomenon. Signs and symptoms are usually intermittent and mild; however, sequelae have included digital ulceration and/or soft tissue breakdown. Effects of peripheral vasculopathy, including Raynaud’s phenomenon, were observed in post-marketing reports and at the therapeutic dosages of CNS stimulants in all age groups throughout the course of treatment. Signs and symptoms generally improved after dosage reduction or discontinuation of the CNS stimulant.

Careful observation for digital changes is necessary during Methylphenidate HCl Extended-Release Tablets treatment. Further clinical evaluation (e.g., rheumatology referral) may be appropriate for Methylphenidate HCl Extended-Release Tablets-treated patients who develop signs or symptoms of peripheral vasculopathy.

5.8 Long-Term Suppression of Growth in Pediatric Patients

Methylphenidate HCl Extended-Release Tablets are not approved for use and are not recommended in pediatric patients below 6 years of age [see Use in Specific Populations (8.4)].

CNS stimulants have been associated with weight loss and slowing of growth rate in pediatric patients.

Careful follow-up of weight and height in children ages 7 to 10 years who were randomized to either methylphenidate or nonmedication treatment groups over 14 months, as well as in naturalistic subgroups of newly methylphenidate-treated and nonmedication-treated children over 36 months (to the ages of 10 to 13 years), suggests that pediatric patients who received methylphenidate for 7 days per week throughout the year had a temporary slowing in growth rate (on average, a total of about 2 cm less growth in height and 2.7 kg less growth in weight over 3 years), without evidence of growth rebound during this development period. Closely monitor growth (weight and height) in Methylphenidate HCl Extended-Release Tablets-treated pediatric patients. Pediatric patients who are not growing or gaining height or weight as expected may need to have their treatment interrupted.

5.9 Potential for Gastrointestinal Obstruction

Because the Methylphenidate HCl Extended-Release Tablet is nondeformable and does not appreciably change in shape in the GI tract, Methylphenidate HCl Extended-Release Tablets should not ordinarily be administered to patients with preexisting severe gastrointestinal narrowing (pathologic or iatrogenic, for example: esophageal motility disorders, small bowel inflammatory disease, “short gut” syndrome due to adhesions or decreased transit time, past history of peritonitis, cystic fibrosis, chronic intestinal pseudo-obstruction, or Meckel’s diverticulum). There have been rare reports of obstructive symptoms in patients with known strictures in association with the ingestion of drugs in nondeformable controlled-release formulations. Due to the controlled-release design of the tablet, Methylphenidate HCl Extended-Release Tablets should only be used in patients who are able to swallow the tablet whole [see Patient Counseling Information (17)].

5.10 Hematologic Monitoring

Periodic CBC, differential, and platelet counts are advised during prolonged therapy.

5.11 Acute Angle Closure Glaucoma

There have been rare reports of angle closure glaucoma associated with methylphenidate treatment.

Although the mechanism is not clear, Methylphenidate HCl Extended-Release Tablets-treated patients considered at risk for acute angle closure glaucoma (e.g., patients with significant hyperopia) should be evaluated by an ophthalmologist.

5.12 Increased Intraocular Pressure and Glaucoma

There have been reports of an elevation of intraocular pressure (IOP) associated with methylphenidate treatment [see Adverse Reactions (6.5)].

Prescribe Methylphenidate HCl Extended-Release Tablets to patients with open-angle glaucoma or abnormally increased IOP only if the benefit of treatment is considered to outweigh the risk. Closely monitor Methylphenidate HCl Extended-Release Tablets-treated patients with a history of abnormally increased IOP or open angle glaucoma.

5.13 Motor and Verbal Tics, and Worsening of Tourette’s Syndrome

CNS stimulants, including methylphenidate, have been associated with the onset or exacerbation of motor and verbal tics [see Adverse Reactions (6.2, 6.5)]. Worsening of Tourette’s syndrome has also been reported.

Before initiating Methylphenidate HCl Extended-Release Tablets, assess the family history and clinically evaluate patients for tics or Tourette’s syndrome. Regularly monitor Methylphenidate HCl Extended-Release Tablets-treated patients for the emergence or worsening of tics or Tourette’s syndrome, and discontinue treatment if clinically appropriate.

6 ADVERSE REACTIONS

The following are discussed in more detail in other sections of the labeling:

- Abuse, Misuse, and Addiction [see Boxed Warning, Warnings and Precautions (5.1)]
- Hypersensitivity to Methylphenidate [see Contraindications (4.1)]
- Monoamine Oxidase Inhibitors [see Contraindications (4.2) and Drug Interactions (7.1)]
- Risks to Patients with Serious Cardiac Disease [see Warnings and Precautions (5.2)]
- Increased Blood Pressure and Heart Rate [see Warnings and Precautions (5.3)]
- Psychiatric Adverse Reactions [see Warnings and Precautions (5.4)]
- Seizures [see Warnings and Precautions (5.5)]
- Priapism [see Warnings and Precautions (5.6)]
- Peripheral Vasculopathy, including Raynaud’s Phenomenon [see Warnings and Precautions (5.7)]
- Long-Term Suppression of Growth in Pediatric Patients [see Warnings and Precautions (5.8)]
- Potential for Gastrointestinal Obstruction [see Warnings and Precautions (5.9)]
- Hematologic Monitoring [see Warnings and Precautions (5.10)]
- Acute Angle Closure Glaucoma [see Warnings and Precautions (5.11)]
- Increased Intraocular Pressure and Glaucoma [see Warnings and Precautions (5.12)]
- Motor and Verbal Tics, and Worsening of Tourette’s Syndrome [see Warnings and Precautions (5.13)]

The most common adverse reaction in double-blind clinical trials (>5%) in pediatric patients (children and adolescents) was abdominal pain upper. The most common adverse reactions in double-blind clinical trials (>5%) in adult patients were decreased appetite, headache, dry mouth, nausea, insomnia, anxiety, dizziness, weight decreased, irritability, and hyperhidrosis [see Adverse Reactions (6.1)].

The most common adverse reactions associated with discontinuation (≥1%) from either pediatric or adult clinical trials were anxiety, irritability, insomnia, and blood pressure increased [see Adverse Reactions (6.3)].

The development program for Methylphenidate HCl Extended-Release Tablets included exposures in a total of 3906 participants in clinical trials. Children, adolescents, and adults with ADHD were evaluated in 6 controlled clinical studies and 11 open-label clinical studies (see Table 3). Safety was assessed by collecting adverse events, vital signs, weights, ECGs, and by performing physical examinations and laboratory analyses.

Table 3. Methylphenidate HCl Extended-Release Tablets Exposure in Double-Blind and Open-Label Clinical Studies
Patient Population | N | Dose Range
Children | 2216 | 18 to 54 mg once daily
Adolescents | 502 | 18 to 72 mg once daily
Adults | 1188 | 18 to 108 mg once daily

Adverse events during exposure were obtained primarily by general inquiry and recorded by clinical investigators using their own terminology. Consequently, to provide a meaningful estimate of the proportion of individuals experiencing adverse events, events were grouped in standardized categories using MedDRA terminology.

The stated frequencies of adverse events represent the proportion of individuals who experienced, at least once, a treatment-emergent adverse event of the type listed. An event was considered treatment-emergent if it occurred for the first time or worsened while receiving therapy following baseline evaluation.

Throughout this section, adverse reactions are reported. Adverse reactions are adverse events that were considered to be reasonably associated with the use of Methylphenidate HCl Extended-Release Tablets based on the comprehensive assessment of the available adverse event information. A causal association for Methylphenidate HCl Extended-Release Tablets often cannot be reliably established in individual cases. Further, because clinical trials are conducted under widely varying conditions, adverse reaction rates observed in the clinical trials of a drug cannot be directly compared to rates in clinical trials of another drug and may not reflect the rates observed in clinical practice.

The majority of adverse reactions were mild to moderate in severity.

6.1 Commonly Observed Adverse Reactions in Double-Blind, Placebo-Controlled Clinical Trials

Adverse reactions in either the pediatric or adult double-blind adverse reactions tables may be relevant for both patient populations.

Children and Adolescents

Table 4 lists the adverse reactions reported in 1% or more of Methylphenidate HCl Extended-Release Tablets-treated children and adolescent subjects in 4 placebo-controlled, double-blind clinical trials.

Table 4. Adverse Reactions Reported by ≥1% of Methylphenidate HCl Extended-Release Tablets-Treated Children and Adolescent Subjects in 4 Placebo-Controlled, Double-Blind Clinical Trials of Methylphenidate HCl Extended-Release Tablets
System/Organ Class Adverse Reaction | Methylphenidate HCl Extended-Release Tablets (n=321) % | Placebo (n=318) %
Gastrointestinal Disorders
Abdominal pain upper | 6.2 | 3.8
Vomiting | 2.8 | 1.6
General Disorders and Administration Site Conditions
Pyrexia | 2.2 | 0.9
Infections and Infestations
Nasopharyngitis | 2.8 | 2.2
Nervous System Disorders
Dizziness | 1.9 | 0
Psychiatric Disorders
Insomnia [Terms of Initial insomnia (Methylphenidate=0.6%) and Insomnia (Methylphenidate=2.2%) are combined into Insomnia.] | 2.8 | 0.3
Respiratory, Thoracic and Mediastinal Disorders
Cough | 1.9 | 0.9
Oropharyngeal pain | 1.2 | 0.9

The majority of adverse reactions were mild to moderate in severity.

Adults

Table 5 lists the adverse reactions reported in 1% or more of Methylphenidate HCl Extended-Release Tablets-treated adults in 2 placebo-controlled, double-blind clinical trials.

Table 5. Adverse Reactions Reported by ≥1% of Methylphenidate HCl Extended-Release Tablets-Treated Adult Subjects in 2 Placebo-Controlled, Double-Blind Clinical Trials [Included doses up to 108 mg.]
System/Organ Class Adverse Reaction | Methylphenidate HCl Extended-Release Tablets (n=415) % | Placebo (n=212) %
Cardiac Disorders
Tachycardia | 4.8 | 0
Palpitations | 3.1 | 0.9
Ear and Labyrinth Disorders
Vertigo | 1.7 | 0
Eye Disorders
Vision blurred | 1.7 | 0.5
Gastrointestinal Disorders
Dry mouth | 14.0 | 3.8
Nausea | 12.8 | 3.3
Dyspepsia | 2.2 | 0.9
Vomiting | 1.7 | 0.5
Constipation | 1.4 | 0.9
General Disorders and Administration Site Conditions
Irritability | 5.8 | 1.4
Infections and Infestations
Upper respiratory tract infection | 2.2 | 0.9
Investigations
Weight decreased | 6.5 | 3.3
Metabolism and Nutrition Disorders
Decreased appetite | 25.3 | 6.6
Anorexia | 1.7 | 0
Musculoskeletal and Connective Tissue Disorders
Muscle tightness | 1.9 | 0
Nervous System Disorders
Headache | 22.2 | 15.6
Dizziness | 6.7 | 5.2
Tremor | 2.7 | 0.5
Paresthesia | 1.2 | 0
Sedation | 1.2 | 0
Tension headache | 1.2 | 0.5
Psychiatric Disorders
Insomnia | 12.3 | 6.1
Anxiety | 8.2 | 2.4
Initial insomnia | 4.3 | 2.8
Depressed mood | 3.9 | 1.4
Nervousness | 3.1 | 0.5
Restlessness | 3.1 | 0
Agitation | 2.2 | 0.5
Aggression | 1.7 | 0.5
Bruxism | 1.7 | 0.5
Depression | 1.7 | 0.9
Libido decreased | 1.7 | 0.5
Affect lability | 1.4 | 0.9
Confusional state | 1.2 | 0.5
Tension | 1.2 | 0.5
Respiratory, Thoracic and Mediastinal Disorders
Oropharyngeal pain | 1.7 | 1.4
Skin and Subcutaneous Tissue Disorders
Hyperhidrosis | 5.1 | 0.9

The majority of ADRs were mild to moderate in severity.

6.2 Other Adverse Reactions Observed in Methylphenidate HCl Extended-Release Tablets Clinical Trials

This section includes adverse reactions reported by Methylphenidate HCl Extended-Release Tablets-treated subjects in double-blind trials that do not meet the criteria specified for Table 4 or Table 5 and all adverse reactions reported by Methylphenidate HCl Extended-Release Tablets -treated subjects who participated in open-label and postmarketing clinical trials.

Blood and Lymphatic System Disorders: Leukopenia

Eye Disorders: Accommodation disorder, Dry eye

Vascular Disorders: Hot flush

Gastrointestinal Disorders: Abdominal discomfort, Abdominal pain, Diarrhea

General Disorders and Administrative Site Conditions: Asthenia, Fatigue, Feeling jittery, Thirst

Infections and Infestations: Sinusitis

Investigations: Alanine aminotransferase increased, Blood pressure increased, Cardiac murmur, Heart rate increased

Musculoskeletal and Connective Tissue Disorders: Muscle spasms

Nervous System Disorders: Lethargy, Psychomotor hyperactivity, Somnolence

Psychiatric Disorders: Anger, Hypervigilance, Mood altered, Mood swings, Panic attack, Sleep disorder, Tearfulness, Tic

Reproductive System and Breast Disorders: Erectile dysfunction

Respiratory, Thoracic and Mediastinal Disorders: Dyspnea

Skin and Subcutaneous Tissue Disorders: Rash, Rash macular

Vascular Disorders: Hypertension

6.3 Discontinuation Due to Adverse Reactions

Adverse reactions in the 4 placebo-controlled studies of children and adolescents leading to discontinuation occurred in 2 Methylphenidate HCl Extended-Release Tablets patients (0.6%) including depressed mood (1, 0.3%) and headache and insomnia (1, 0.3%), and 6 placebo patients (1.9%) including headache and insomnia (1, 0.3%), irritability (2, 0.6%), headache (1, 0.3%), psychomotor hyperactivity (1, 0.3%), and tic (1, 0.3%).

In the 2 placebo-controlled studies of adults, 25 Methylphenidate HCl Extended-Release Tablets patients (6.0%) and 6 placebo patients (2.8%) discontinued due to an adverse reaction. Those events with an incidence of >0.5% in the Methylphenidate HCl Extended-Release Tablets patients included anxiety (1.7%), irritability (1.4%), blood pressure increased (1.0%), and nervousness (0.7%). In placebo patients, blood pressure increased and depressed mood had an incidence of >0.5% (0.9%).

In the 11 open-label studies of children, adolescents, and adults, 266 Methylphenidate HCl Extended-Release Tablets patients (7.0%) discontinued due to an adverse reaction. Those events with an incidence of >0.5% included insomnia (1.2%), irritability (0.8%), anxiety (0.7%), decreased appetite (0.7%), and tic (0.6%).

6.4 Blood Pressure and Heart Rate Increases

In the laboratory classroom clinical trials in children (Studies 1 and 2), both Methylphenidate HCl Extended-Release Tablets once daily and methylphenidate three times daily increased resting pulse by an average of 2 to 6 bpm and produced average increases of systolic and diastolic blood pressure of roughly 1 to 4 mm Hg during the day, relative to placebo. In the placebo-controlled adolescent trial (Study 4), mean increases from baseline in resting pulse rate were observed with Methylphenidate HCl Extended-Release Tablets and placebo at the end of the double-blind phase (5 and 3 beats/minute, respectively). Mean increases from baseline in blood pressure at the end of the double-blind phase for Methylphenidate HCl Extended-Release Tablets and placebo-treated patients were 0.7 and 0.7 mm Hg (systolic) and 2.6 and 1.4 mm Hg (diastolic), respectively. In one placebo-controlled study in adults (Study 6), dose-dependent mean increases of 3.9 to 9.8 bpm from baseline in standing pulse rate were observed with Methylphenidate HCl Extended-Release Tablets at the end of the double-blind treatment vs. an increase of 2.7 beats/minute with placebo. Mean changes from baseline in standing blood pressure at the end of double-blind treatment ranged from 0.1 to 2.2 mm Hg (systolic) and -0.7 to 2.2 mm Hg (diastolic) for Methylphenidate HCl Extended-Release Tablets and was 1.1 mm Hg (systolic) and -1.8 mm Hg (diastolic) for placebo. In a second placebo-controlled study in adults (Study 5), mean changes from baseline in resting pulse rate were observed for Methylphenidate HCl Extended-Release Tablets and placebo at the end of the double-blind treatment (3.6 and –1.6 beats/minute, respectively). Mean changes from baseline in blood pressure at the end of the double–blind treatment for Methylphenidate HCl Extended-Release Tablets and placebo-treated patients were –1.2 and –0.5 mm Hg (systolic) and 1.1 and 0.4 mm Hg (diastolic), respectively [see Warnings and Precautions (5.3)].

6.5 Postmarketing Experience

The following additional adverse reactions have been identified during postapproval use of Methylphenidate HCl Extended-Release Tablets. Because these reactions are reported voluntarily from a population of uncertain size, it is not always possible to reliably estimate their frequency:

Blood and Lymphatic System Disorders: Pancytopenia, Thrombocytopenia, Thrombocytopenic purpura

Cardiac Disorders: Angina pectoris, Bradycardia, Extrasystoles, Supraventricular tachycardia, Ventricular extrasystoles

Eye Disorders: Diplopia, Increased intraocular pressure, Mydriasis, Visual impairment

General Disorders: Chest pain, Chest discomfort, Drug effect decreased, Hyperpyrexia, Therapeutic response decreased

Hepatobiliary disorders: Hepatocellular injury, Acute hepatic failure

Immune System Disorders: Hypersensitivity reactions such as Angioedema, Anaphylactic reactions, Auricular swelling, Bullous conditions, Exfoliative conditions, Urticarias, Pruritus NEC, Rashes, Eruptions, and Exanthemas NEC

Investigations: Blood alkaline phosphatase increased, Blood bilirubin increased, Hepatic enzyme increased, Platelet count decreased, White blood cell count abnormal

Musculoskeletal, Connective Tissue and Bone Disorders: Arthralgia, Myalgia, Muscle twitching, Rhabdomyolysis

Nervous System Disorders: Convulsion, Grand mal convulsion, Dyskinesia, Serotonin syndrome in combination with serotonergic drugs, Motor and Verbal Tics

Psychiatric Disorders: Disorientation, Hallucination, Hallucination auditory, Hallucination visual, Mania, Logorrhea, Libido changes

Reproductive System and Breast Disorders: Priapism

Skin and Subcutaneous Tissue Disorders: Alopecia, Erythema

Vascular Disorders: Raynaud's phenomenon

7 DRUG INTERACTIONS

7.1 MAO Inhibitors

Methylphenidate HCl Extended-Release Tablets should not be used in patients being treated (currently or within the preceding 2 weeks) with MAO inhibitors [see Contraindications (4.2)].

7.2 Vasopressor Agents

Because of possible increases in blood pressure, Methylphenidate HCl Extended-Release Tablets should be used cautiously with vasopressor agents [see Warnings and Precautions (5.3)].

7.3 Coumarin Anticoagulants, Antidepressants, and Selective Serotonin Reuptake Inhibitors

Human pharmacologic studies have shown that methylphenidate may inhibit the metabolism of coumarin anticoagulants, anticonvulsants (eg, phenobarbital, phenytoin, primidone), and some antidepressants (tricyclics and selective serotonin reuptake inhibitors). Downward dose adjustment of these drugs may be required when given concomitantly with methylphenidate. It may be necessary to adjust the dosage and monitor plasma drug concentrations (or, in the case of coumarin, coagulation times), when initiating or discontinuing concomitant methylphenidate.

7.4 Halogenated Anesthetics

Concomitant use of halogenated anesthetics and Methylphenidate HCl Extended-Release Tablets may increase the risk of sudden blood pressure and heart rate increase during surgery. Monitor blood pressure and avoid use of Methylphenidate HCl Extended-Release Tablets in patients being treated with anesthetics on the day of surgery.

7.5 Risperidone

Combined use of methylphenidate with risperidone when there is a change, whether an increase or decrease, in dosage of either or both medications, may increase the risk of extrapyramidal symptoms (EPS). Monitor for signs of EPS.

8 USE IN SPECIFIC POPULATIONS

8.1 Pregnancy

TERATOGENIC EFFECTS

TERATOGENIC EFFECTS

Pregnancy Category C

Methylphenidate has been shown to have teratogenic effects in rabbits when given in doses of 200 mg/kg/day, which is approximately 100 times and 40 times the maximum recommended human dose on a mg/kg and mg/m^2 basis, respectively.

A reproduction study in rats revealed no evidence of harm to the fetus at oral doses up to 30 mg/kg/day, approximately 15-fold and 3-fold the maximum recommended human dose of Methylphenidate HCl Extended-Release Tablets on a mg/kg and mg/m^2 basis, respectively. The approximate plasma exposure to methylphenidate plus its main metabolite PPAA in pregnant rats was 1-2 times that seen in trials in volunteers and patients with the maximum recommended dose of Methylphenidate HCl Extended-Release Tablets based on the AUC.

The safety of methylphenidate for use during human pregnancy has not been established. There are no adequate and well-controlled studies in pregnant women. Methylphenidate HCl Extended-Release Tablets should be used during pregnancy only if the potential benefit justifies the potential risk to the fetus.

8.2 Labor and Delivery

The effect of Methylphenidate HCl Extended-Release Tablets on labor and delivery in humans is unknown.

8.3 Nursing Mothers

It is not known whether methylphenidate is excreted in human milk. Because many drugs are excreted in human milk, caution should be exercised if Methylphenidate HCl Extended-Release Tablets are administered to a nursing woman.

In lactating female rats treated with a single oral dose of 5 mg/kg radiolabeled methylphenidate, radioactivity (representing methylphenidate and/or its metabolites) was observed in milk and levels were generally similar to those in plasma.

8.4 Pediatric Use

The safety and effectiveness of Methylphenidate HCl Extended-Release Tablets have not been established in pediatric patients below the age of 6 years.

In studies evaluating extended-release methylphenidate products, patients 4 to <6 years of age had higher systemic methylphenidate exposures than those observed in older pediatric patients at the same dosage. Pediatric patients 4 to <6 years of age also had a higher incidence of adverse reactions, including weight loss.

8.5 Geriatric Use

Methylphenidate HCl Extended-Release Tablets have not been studied in patients greater than 65 years of age.

9 DRUG ABUSE AND DEPENDENCE

9.1 Controlled Substance

Methylphenidate HCl Extended-Release Tablets contain methylphenidate, a Schedule II controlled substance.

9.2 Abuse

Methylphenidate HCl Extended-Release Tablets have a high potential for abuse and misuse which can lead to the development of a substance use disorder, including addiction [see Warnings and Precautions (5.1)]. Methylphenidate HCl Extended-Release Tablets can be diverted for non-medical use into illicit channels or distribution.

Abuse is the intentional non-therapeutic use of a drug, even once, to achieve a desired psychological or physiological effect. Misuse is the intentional use, for therapeutic purposes, of a drug by an individual in a way other than prescribed by a health care provider or for whom it was not prescribed. Drug addiction is a cluster of behavioral, cognitive, and physiological phenomena that may include a strong desire to take the drug, difficulties in controlling drug use (e.g., continuing drug use despite harmful consequences, giving a higher priority to drug use than other activities and obligations), and possible tolerance or physical dependence.

Misuse and abuse of methylphenidate may cause increased heart rate, respiratory rate, or blood pressure; sweating; dilated pupils; hyperactivity; restlessness; insomnia; decreased appetite; loss of coordination; tremors; flushed skin; vomiting; and/or abdominal pain.

Anxiety, psychosis, hostility, aggression, and suicidal or homicidal ideation have also been observed with CNS stimulants abuse and/or misuse. Misuse and abuse of CNS stimulants, including Methylphenidate HCl Extended-Release Tablets, can result in overdose and death [see Overdosage (10)], and this risk is increased with higher doses or unapproved methods of administration, such as snorting or injection.

In two placebo-controlled human abuse potential studies, single oral doses of Methylphenidate HCl Extended-Release Tablets were compared to single oral doses of immediate-release methylphenidate (IR MPH) and placebo in subjects with a history of recreational stimulant use to assess relative abuse potential. For the purpose of this assessment, the response for each of the subjective measures was defined as the maximum effect within the first 8 hours after dose administration.

In one study (n=40), both Methylphenidate HCl Extended-Release Tablets (108 mg) and 60 mg IR MPH compared to placebo produced statistically significantly greater responses on the five subjective measures suggestive of abuse potential. In comparisons between the two active treatments, however, Methylphenidate HCl Extended-Release Tablets (108 mg) produced variable responses on positive subjective measures that were either statistically indistinguishable from (Abuse Potential, Drug Liking, Amphetamine, and Morphine Benzedrine Group [Euphoria]) or statistically less than (Stimulation-Euphoria) responses produced by 60 mg IR MPH.

In another study (n=49), both doses of Methylphenidate HCl Extended-Release Tablets (54 mg and 108 mg) and both doses of IR MPH (50 mg and 90 mg) produced statistically significantly greater responses compared to placebo on the two primary scales used in the study (Drug Liking, Euphoria). When doses of Methylphenidate HCl Extended-Release Tablets (54 mg and 108 mg) were compared to IR MPH (50 mg and 90 mg), respectively, Methylphenidate HCl Extended-Release Tablets produced statistically significantly lower subjective responses on these two scales than IR MPH. Methylphenidate HCl Extended-Release Tablets (108 mg) produced responses that were statistically indistinguishable from the responses on these two scales produced by IR MPH (50 mg). Differences in subjective responses to the respective doses should be considered in the context that only 22% of the total amount of methylphenidate in Methylphenidate HCl Extended-Release Tablets is available for immediate release from the drug overcoat [see System Components and Performance (11.1)].

Although these findings reveal a relatively lower response to Methylphenidate HCl Extended-Release Tablets on subjective measures suggestive of abuse potential compared to IR MPH at roughly equivalent total MPH doses, the relevance of these findings to the abuse potential of Methylphenidate HCl Extended-Release Tablets in the community is unknown.

9.3 Dependence

Physical Dependence

Methylphenidate HCl Extended-Release Tablets may produce physical dependence. Physical dependence is a state that develops as a result of physiological adaptation in response to repeated drug use, manifested by withdrawal signs and symptoms after abrupt discontinuation or a significant dose reduction of a drug.

Withdrawal signs and symptoms after abrupt discontinuation or dose reduction following prolonged use of CNS stimulants including Methylphenidate HCl Extended-Release Tablets include dysphoric mood; depression; fatigue; vivid, unpleasant dreams; insomnia or hypersomnia; increased appetite; and psychomotor retardation or agitation.

Tolerance

Methylphenidate HCl Extended-Release Tablets may produce tolerance. Tolerance is a physiological state characterized by a reduced response to a drug after repeated administration (i.e., a higher dose of a drug is required to produce the same effect that was once obtained at a lower dose).

10 OVERDOSAGE

10.1 Clinical Effects of Overdose

Overdose of CNS stimulants is characterized by the following sympathomimetic effects:

- Cardiovascular effects including tachyarrhythmias, and hypertension or hypotension. Vasospasm, myocardial infarction, or aortic dissection may precipitate sudden cardiac death. Takotsubo cardiomyopathy may develop.
- CNS effects including psychomotor agitation, confusion, and hallucinations. Serotonin syndrome, seizures, cerebral vascular accidents, and coma may occur.
- Life-threatening hyperthermia (temperatures greater than 104°F) and rhabdomyolysis may develop.

10.2 Overdose Management

Consider the possibility of multiple drug ingestion. The pharmacokinetic profile of Methylphenidate HCl Extended-Release Tablets should be considered when treating patients with overdose. Because methylphenidate has a large volume of distribution and is rapidly metabolized, dialysis is not useful. Consider contacting the Poison Help line (1-800-222-1222) or a medical toxicologist for additional overdose management recommendations.

11 DESCRIPTION

Methylphenidate HCl Extended-Release Tablets, USP are a central nervous system (CNS) stimulant. Methylphenidate HCl Extended-Release Tablets, USP are available in four tablet strengths. Each extended-release tablet for once-a-day oral administration contains 18, 27, 36, or 54 mg of methylphenidate HCl USP and is designed to have a 12-hour duration of effect. Chemically, methylphenidate HCl is d,l (racemic) methyl α-phenyl-2-piperidineacetate hydrochloride. Its empirical formula is C14H19NO2•HCl. Its structural formula is:

Methylphenidate HCl USP is a white, odorless crystalline powder. Its solutions are acid to litmus. It is freely soluble in water and in methanol, soluble in alcohol, and slightly soluble in chloroform and in acetone. Its molecular weight is 269.77.

Methylphenidate HCl Extended-Release Tablets, USP also contains the following inert ingredients: carboxymethylcellulose sodium, colloidal silicon dioxide, corn starch, ethocel, hydroxypropyl cellulose, hypromellose, hypromellose acetate succinate, magnesium stearate, microcrystalline cellulose, polyethylene glycol, sucrose, talc, titanium dioxide and triethyl citrate. The 18, 36, and 54 mg tablets also contain synthetic red iron oxide. The 27 mg tablets also contain yellow iron oxide.

Methylphenidate HCl Extended-Release Tablets meet USP Dissolution Test 3.

11.1 System Components and Performance

Methylphenidate HCl Extended-Release Tablets uses extended-release bead technology to deliver methylphenidate HCl at a controlled rate. The system, which resembles a conventional tablet in appearance, is comprised of a tablet core containing the extended-release beads and the core is covered with an immediate-release drug overcoat. In an aqueous environment, such as the gastrointestinal tract, the drug overcoat dissolves within one hour, providing an initial dose of methylphenidate. The tablet disintegrates and then polymer coatings on the beads control the release of methylphenidate HCl over the 12 hour dosing period.

12 CLINICAL PHARMACOLOGY

12.1 Mechanism of Action

Methylphenidate HCl is a central nervous system (CNS) stimulant. The mode of therapeutic action in Attention Deficit Hyperactivity Disorder (ADHD) is not known. Methylphenidate is thought to block the reuptake of norepinephrine and dopamine into the presynaptic neuron and increase the release of these monoamines into the extraneuronal space.

12.2 Pharmacodynamics

Methylphenidate is a racemic mixture comprised of the d- and l-isomers. The d-isomer is more pharmacologically active than the l-isomer.

12.3 Pharmacokinetics

Absorption

Methylphenidate is readily absorbed. Following oral administration of Methylphenidate HCl Extended-Release Tablets, plasma methylphenidate concentrations increase rapidly, reaching an initial maximum at about 1 hour, followed by gradual ascending concentrations over the next 5 to 9 hours, after which a gradual decrease begins. Mean times to reach peak plasma concentrations across all doses of Methylphenidate HCl Extended-Release Tablets occurred between 6 and 10 hours.

Methylphenidate HCl Extended-Release Tablets once daily minimizes the fluctuations between peak and trough concentrations associated with immediate-release methylphenidate three times daily (see Figure 1). The relative bioavailability of Methylphenidate HCl Extended-Release Tablets once daily and methylphenidate three times daily in adults is comparable.

Figure 1. Mean methylphenidate plasma concentrations in 36 adults, following a single dose of Methylphenidate HCl Extended-Release Tablets 18 mg once daily and immediate-release methylphenidate 5 mg three times daily administered every 4 hours.

The mean single-dose pharmacokinetic parameters in 36 healthy adults following the administration of Methylphenidate HCl Extended-Release Tablets 18 mg once daily and methylphenidate 5 mg three times daily are summarized in Table 6.

Table 6. Pharmacokinetic Parameters (Mean ± SD) After Single Dose in Healthy Adults
Parameters | Methylphenidate HCl Extended-Release Tablets (18 mg once daily) (n=36) | Methylphenidate (5 mg three times daily) (n=35)
Cmax (ng/mL) | 3.7 ± 1.0 | 4.2 ± 1.0
Tmax (h) | 6.8 ± 1.8 | 6.5 ± 1.8
AUCinf (ng∙h/mL) | 41.8 ± 13.9 | 38.0 ± 11.0
t1/2 (h) | 3.5 ± 0.4 | 3.0 ± 0.5

The pharmacokinetics of Methylphenidate HCl Extended-Release Tablets were evaluated in healthy adults following single- and multiple-dose administration (steady state) of doses up to 144 mg/day. The mean half-life was about 3.6 hours. No differences in the pharmacokinetics of Methylphenidate HCl Extended-Release Tablets were noted following single and repeated once-daily dosing, indicating no significant drug accumulation. The AUC and t1/2 following repeated once-daily dosing are similar to those following the first dose of Methylphenidate HCl Extended-Release Tablets in a dose range of 18 to 144 mg.

Dose Proportionality

Following administration of Methylphenidate HCl Extended-Release Tablets in single doses of 18, 36, and 54 mg/day to healthy adults, Cmax and AUC (0-inf) of d-methylphenidate were proportional to dose, whereas l-methylphenidate Cmax and AUC (0-inf) increased disproportionately with respect to dose. Following administration of Methylphenidate HCl Extended-Release Tablets, plasma concentrations of the l-isomer were approximately 1/40th the plasma concentrations of the d-isomer.

In healthy adults, single and multiple dosing of once-daily Methylphenidate HCl Extended-Release Tablets doses from 54 to 144 mg/day resulted in linear and dose-proportional increases in Cmax and AUCinf for total methylphenidate (MPH) and its major metabolite, α-phenyl-piperidine acetic acid (PPAA). There was no time dependency in the pharmacokinetics of methylphenidate. The ratio of metabolite (PPAA) to parent drug (MPH) was constant across doses from 54 to 144 mg/day, both after single dose and upon multiple dosing.

In a multiple-dose study in adolescent ADHD patients aged 13 to 16 administered their prescribed dose (18 to 72 mg/day) of Methylphenidate HCl Extended-Release Tablets, mean Cmax and AUCTAU of d- and total methylphenidate increased proportionally with respect to dose.

Distribution

Plasma methylphenidate concentrations in adults and adolescents decline biexponentially following oral administration. The half-life of methylphenidate in adults and adolescents following oral administration of Methylphenidate HCl Extended-Release Tablets was approximately 3.5 hours.

Metabolism and Excretion

In humans, methylphenidate is metabolized primarily by de-esterification to PPAA, which has little or no pharmacologic activity. In adults the metabolism of Methylphenidate HCl Extended-Release Tablets once daily as evaluated by metabolism to PPAA is similar to that of methylphenidate three times daily. The metabolism of single and repeated once-daily doses of Methylphenidate HCl Extended-Release Tablets is similar.

After oral dosing of radiolabeled methylphenidate in humans, about 90% of the radioactivity was recovered in urine. The main urinary metabolite was PPAA, accounting for approximately 80% of the dose.

Food Effects

In patients, there were no differences in either the pharmacokinetics or the pharmacodynamic performance of Methylphenidate HCl Extended-Release Tablets when administered after a high-fat breakfast. There is no evidence of dose dumping in the presence or absence of food.

Alcohol Effect

An in vitro study was conducted to explore the effect of alcohol on the release characteristics of methylphenidate from the Methylphenidate HCl Extended-Release 18 mg tablet dosage form. At an alcohol concentration up to 40% there was no increased release of methylphenidate in the first hour. The results with the 18 mg tablet strength are considered representative of the other available tablet strengths.

Special Populations

Gender

In healthy adults, the mean dose-adjusted AUC(0-inf) values for Methylphenidate HCl Extended-Release Tablets were 36.7 ng•h/mL in men and 37.1 ng•h/mL in women, with no differences noted between the two groups.

Race

In adults receiving Methylphenidate HCl Extended-Release Tablets, dose-adjusted AUC(0-inf) was consistent across ethnic groups; however, the sample size may have been insufficient to detect ethnic variations in pharmacokinetics.

Age

Increase in age resulted in increased apparent oral clearance (CL/F) (58% increase in adolescents compared to children). Some of these differences could be explained by body-weight differences among these populations. This suggests that subjects with higher body-weight may have lower exposures of total methylphenidate at similar doses.

The pharmacokinetics of Methylphenidate HCl Extended-Release Tablets have not been studied in children less than 6 years of age.

Renal Insufficiency

There is no experience with the use of Methylphenidate HCl Extended-Release Tablets in patients with renal insufficiency. After oral administration of radiolabeled methylphenidate in humans, methylphenidate was extensively metabolized and approximately 80% of the radioactivity was excreted in the urine in the form of PPAA. Since renal clearance is not an important route of methylphenidate clearance, renal insufficiency is expected to have little effect on the pharmacokinetics of Methylphenidate HCl Extended-Release Tablets.

Hepatic Insufficiency

There is no experience with the use of Methylphenidate HCl Extended-Release Tablets in patients with hepatic insufficiency.

13 NONCLINICAL TOXICOLOGY

13.1 Carcinogenesis, Mutagenesis, and Impairment of Fertility

Carcinogenesis

In a lifetime carcinogenicity study carried out in B6C3F1 mice, methylphenidate caused an increase in hepatocellular adenomas and, in males only, an increase in hepatoblastomas at a daily dose of approximately 60 mg/kg/day. This dose is approximately 30 times and 4 times the maximum recommended human dose of Methylphenidate HCl Extended-Release Tablets on a mg/kg and mg/m^2 basis, respectively. Hepatoblastoma is a relatively rare rodent malignant tumor type. There was no increase in total malignant hepatic tumors. The mouse strain used is sensitive to the development of hepatic tumors, and the significance of these results to humans is unknown.

Methylphenidate did not cause any increases in tumors in a lifetime carcinogenicity study carried out in F344 rats; the highest dose used was approximately 45 mg/kg/day, which is approximately 22 times and 5 times the maximum recommended human dose of Methylphenidate HCl Extended-Release Tablets on a mg/kg and mg/m^2 basis, respectively.

In a 24-week carcinogenicity study in the transgenic mouse strain p53+/-, which is sensitive to genotoxic carcinogens, there was no evidence of carcinogenicity. Male and female mice were fed diets containing the same concentration of methylphenidate as in the lifetime carcinogenicity study; the high-dose groups were exposed to 60 to 74 mg/kg/day of methylphenidate.

Mutagenesis

Methylphenidate was not mutagenic in the in vitro Ames reverse mutation assay or the in vitro mouse lymphoma cell forward mutation assay. Sister chromatid exchanges and chromosome aberrations were increased, indicative of a weak clastogenic response, in an in vitro assay in cultured Chinese Hamster Ovary cells. Methylphenidate was negative in vivo in males and females in the mouse bone marrow micronucleus assay.

Impairment of Fertility

Methylphenidate did not impair fertility in male or female mice that were fed diets containing the drug in an 18-week Continuous Breeding study. The study was conducted at doses up to 160 mg/kg/day, approximately 80-fold and 8-fold the highest recommended human dose of Methylphenidate HCl Extended-Release Tablets on a mg/kg and mg/m^2 basis, respectively.

14 CLINICAL STUDIES

Methylphenidate HCl Extended-Release Tablets were demonstrated to be effective in the treatment of Attention Deficit Hyperactivity Disorder (ADHD) in 4 randomized, double-blind, placebo-controlled studies in children and adolescents and 2 double-blind placebo-controlled studies in adults who met the Diagnostic and Statistical Manual 4th edition (DSM-IV) criteria for ADHD.

14.1 Children

Three double-blind, active- and placebo-controlled studies were conducted in 416 children aged 6 to 12 years. The controlled studies compared Methylphenidate HCl Extended-Release Tablets given once daily (18, 36, or 54 mg), methylphenidate given three times daily over 12 hours (15, 30, or 45 mg total daily dose), and placebo in two single-center, 3-week crossover studies (Studies 1 and 2) and in a multicenter, 4-week, parallel-group comparison (Study 3). The primary comparison of interest in all three trials was Methylphenidate HCl Extended-Release Tablets versus placebo.

Symptoms of ADHD were evaluated by community schoolteachers using the Inattention/Overactivity with Aggression (IOWA) Conners scale. Statistically significant reduction in the Inattention/Overactivity subscale versus placebo was shown consistently across all three controlled studies for Methylphenidate HCl Extended-Release Tablets. The scores for Methylphenidate HCl Extended-Release Tablets and placebo for the three studies are presented in Figure 2.

Figure 2. Mean Community School Teacher IOWA Conners Inattention/Overactivity Scores with Methylphenidate HCl Extended-Release Tablets once daily (18, 36, or 54 mg) and placebo. Studies 1 and 2 involved a 3-way crossover of 1 week per treatment arm. Study 3 involved 4 weeks of parallel-group treatments with a Last Observation Carried Forward analysis at week 4. Error bars represent the mean plus standard error of the mean.

In Studies 1 and 2, symptoms of ADHD were evaluated by laboratory schoolteachers using the SKAMP^1 laboratory school rating scale. The combined results from these two studies demonstrated statistically significant improvements in attention and behavior in patients treated with Methylphenidate HCl Extended-Release Tablets versus placebo that were maintained through 12 hours after dosing. Figure 3 presents the laboratory schoolteacher SKAMP ratings for Methylphenidate HCl Extended-Release Tablets and placebo.

^1Swanson, Kotkin, Agler, M-Fynn, and Pelham

Figure 3. Laboratory School Teacher SKAMP Ratings: Mean (SEM) of Combined Attention (Studies 1 and 2)

14.2 Adolescents

In a randomized, double-blind, multicenter, placebo-controlled trial (Study 4) involving 177 patients, Methylphenidate HCl Extended-Release Tablets was demonstrated to be effective in the treatment of ADHD in adolescents aged 13 to 18 years at doses up to 72 mg/day (1.4 mg/kg/day). Of 220 patients who entered an open 4-week titration phase, 177 were titrated to an individualized dose (maximum of 72 mg/day) based on meeting specific improvement criteria on the ADHD Rating Scale and the Global Assessment of Effectiveness with acceptable tolerability. Patients who met these criteria were then randomized to receive either their individualized dose of Methylphenidate HCl Extended-Release Tablets (18 – 72 mg/day, n=87) or placebo (n=90) during a two-week double-blind phase. At the end of this phase, mean scores for the investigator rating on the ADHD Rating Scale demonstrated that Methylphenidate HCl Extended-Release Tablets was statistically significantly superior to placebo.

14.3 Adults

Two double-blind, placebo-controlled studies were conducted in 627 adults aged 18 to 65 years. The controlled studies compared Methylphenidate HCl Extended-Release Tablets administered once daily and placebo in a multicenter, parallel-group, 7-week dose-titration study (Study 5) (36 to 108 mg/day) and in a multicenter, parallel-group, 5-week, fixed-dose study (Study 6) (18, 36, and 72 mg/day).

Study 5 demonstrated the effectiveness of Methylphenidate HCl Extended-Release Tablets in the treatment of ADHD in adults aged 18 to 65 years at doses from 36 mg/day to 108 mg/day based on the change from baseline to final study visit on the Adult ADHD Investigator Rating Scale (AISRS). Of 226 patients who entered the 7-week trial, 110 were randomized to Methylphenidate HCl Extended-Release Tablets and 116 were randomized to placebo. Treatment was initiated at 36 mg/day and patients continued with incremental increases of 18 mg/day (36 to 108 mg/day) based on meeting specific improvement criteria with acceptable tolerability. At the final study visit, mean change scores (LS Mean, SEM) for the investigator rating on the AISRS demonstrated that Methylphenidate HCl Extended-Release Tablets was statistically significantly superior to placebo.

Study 6 was a multicenter, double-blind, randomized, placebo-controlled, parallel-group, dose-response study (5-week duration) with 3 fixed-dose groups (18, 36, and 72 mg). Patients were randomized to receive Methylphenidate HCl Extended-Release Tablets administered at doses of 18 mg (n=101), 36 mg (n=102), 72 mg/day (n=102), or placebo (n=96). All three doses of Methylphenidate HCl Extended-Release Tablets were statistically significantly more effective than placebo in improving CAARS (Conners' Adult ADHD Rating Scale) total scores at double-blind end point in adult subjects with ADHD.

16 HOW SUPPLIED/STORAGE AND HANDLING

Methylphenidate HCl Extended-Release Tablets, USP are available in 18 mg, 27 mg, 36 mg, and 54 mg dosage strengths. The 18 mg tablets are pink and imprinted with “18”, 27 mg tablets are yellow and imprinted with “27”, 36 mg tablets are pink and imprinted with “36”, and 54 mg tablets are pink and imprinted with “54”. All four dosage strengths are supplied in bottles containing 100 tablets.

18 mg | 100 count bottle | NDC 62175-310-37
27 mg | 100 count bottle | NDC 62175-311-37
36 mg | 100 count bottle | NDC 62175-312-37
54 mg | 100 count bottle | NDC 62175-313-37

Storage and Handling

Store at 25°C (77°F); excursions permitted to 15-30°C (59-86°F) [see USP Controlled Room Temperature]. Protect from humidity.

17 PATIENT COUNSELING INFORMATION

Advise the patient to read the FDA-approved patient labeling (Medication Guide).

Abuse, Misuse, and Addiction

Educate patients and their families about the risks of abuse, misuse, and addiction of Methylphenidate HCl Extended-Release Tablets, which can lead to overdose and death, and proper disposal of any unused drug [see Warnings and Precautions (5.1), Drug Abuse and Dependence (9.2), Overdosage (10)]. Advise patients to store Methylphenidate HCl Extended-Release Tablets in a safe place, preferably locked, and instruct patients to not give Methylphenidate HCl Extended-Release Tablets to anyone else.

Risks to Patients with Serious Cardiac Disease

Advise patients that there are potential risks to patients with serious cardiac disease, including sudden death, with Methylphenidate HCl Extended-Release Tablets use. Instruct patients to contact a healthcare provider immediately if they develop symptoms such as exertional chest pain, unexplained syncope, or other symptoms suggestive of cardiac disease [see Warnings and Precautions (5.2)].

Increased Blood Pressure and Heart Rate

Advise patients that Methylphenidate HCl Extended-Release Tablets can cause elevations in blood pressure and heart rate [see Warnings and Precautions (5.3)].

Psychiatric Risks

Advise patients that Methylphenidate HCl Extended-Release Tablets, at recommended doses, can cause psychotic or manic symptoms, even in patients without a prior history of psychotic symptoms or mania [see Warnings and Precautions (5.4)].

Priapism

Advise patients, caregivers, and family members of the possibility of painful or prolonged penile erections (priapism). Instruct the patient to seek immediate medical attention in the event of priapism [see Warnings and Precautions (5.6)].

Circulation Problems in Fingers and Toes [Peripheral Vasculopathy, including Raynaud’s Phenomenon]

Instruct patients beginning treatment with Methylphenidate HCl Extended-Release Tablets about the risk of peripheral vasculopathy, including Raynaud’s phenomenon, and associated signs and symptoms: fingers or toes may feel numb, cool, painful, and/or may change color from pale, to blue, to red.

Instruct patients to report to their physician any new numbness, pain, skin color change, or sensitivity to temperature in fingers or toes.

Instruct patients to call their physician immediately with any signs of unexplained wounds appearing on fingers or toes while taking Methylphenidate HCl Extended-Release Tablets.

Further clinical evaluation (e.g., rheumatology referral) may be appropriate for certain patients.

Suppression of Growth

Advise patients, caregivers, and family members that Methylphenidate HCl Extended-Release Tablets may cause slowing of growth and weight loss [see Warnings and Precautions (5.8)].

Increased Intraocular Pressure (IOP) and Glaucoma

Advise patients that IOP and glaucoma may occur during treatment with Methylphenidate HCl Extended-Release Tablets [see Warnings and Precautions (5.12)].

Motor and Verbal Tics, and Worsening of Tourette’s Syndrome

Advise patients that motor and verbal tics and worsening of Tourette’s Syndrome may occur during treatment with Methylphenidate HCl Extended-Release Tablets. Instruct patients to notify their healthcare provider if emergence of new tics or worsening of tics or Tourette’s syndrome occurs [see Warnings and Precautions (5.13)].

Administration Instructions

Patients should be informed that Methylphenidate HCl Extended-Release Tablets should be swallowed whole with the aid of liquids. Tablets should not be chewed, divided, or crushed.

For more information call 1-844-834-0530.

Manufactured by:

Kremers Urban Pharmaceuticals Inc.

Seymour, IN 47274

CIA75858L

Rev. 01/2026

MEDICATION GUIDE

Methylphenidate (meth” il fen’ i date) HCl Extended-Release Tablets, USP

CII

What is the most important information I should know about Methylphenidate HCl Extended-Release Tablets?

Methylphenidate HCl Extended-Release Tablets may cause serious side effects, including:

- Abuse, misuse, and addiction. Methylphenidate HCl Extended-Release Tablets have a high chance for abuse and misuse and may lead to substance use problems, including addiction. Misuse and abuse of Methylphenidate HCl Extended-Release Tablets, other methylphenidate containing medicines, and amphetamine containing medicines, can lead to overdose and death. The risk of overdose and death is increased with higher doses of Methylphenidate HCl Extended-Release Tablets or when it is used in ways that are not approved, such as snorting or injection.
  - Your healthcare provider should check you or your child’s risk for abuse, misuse, and addiction before starting treatment with Methylphenidate HCl Extended-Release Tablets and will monitor you or your child during treatment.
  - Methylphenidate HCl Extended-Release Tablets may lead to physical dependence after prolonged use, even if taken as directed by your healthcare provider.
  - Do not give Methylphenidate HCl Extended-Release Tablets to anyone else. See “What is Methylphenidate HCl Extended-Release Tablets?” for more information.
  - Keep Methylphenidate HCl Extended-Release Tablets in a safe place and properly dispose of any unused medicine. See “How should I store Methylphenidate HCl Extended-Release Tablets?” for more information.
  - Tell your healthcare provider if you or your child have ever abused or been dependent on alcohol, prescription medicines, or street drugs.
- Risks for people with serious heart disease. Sudden death has happened in people who have heart defects or other serious heart disease.
  Your healthcare provider should check you or your child carefully for heart problems before starting treatment with Methylphenidate HCl Extended-Release Tablets. Tell your healthcare provider if you or your child have any heart problems, heart disease, or heart defects.
  Call your healthcare provider or go to the nearest hospital emergency room right away if you or your child have any signs of heart problems such as chest pain, shortness of breath, or fainting during treatment with Methylphenidate HCl Extended-Release Tablets.
- Increased blood pressure and heart rate.
  Your healthcare provider should check your or your child’s blood pressure and heart rate regularly during treatment with Methylphenidate HCl Extended-Release Tablets.
- Mental (psychiatric) problems, including:

- new or worse behavior or thought problems
- new or worse bipolar illness
- new psychotic symptoms (such as hearing voices, or seeing or believing things that are not real) or new manic symptoms

Tell your healthcare provider about any mental problems you or your child have, or about a family history of suicide, bipolar illness, or depression.

Call your healthcare provider right away if you or your child have any new or worsening mental symptoms or problems during treatment with Methylphenidate HCl Extended-Release Tablets, especially hearing voices, seeing or believing things that are not real, or new manic symptoms.

What is Methylphenidate HCl Extended-Release Tablets?

Methylphenidate HCl Extended-Release Tablets are a central nervous system (CNS) stimulant prescription medicine used for the treatment of Attention Deficit and Hyperactivity Disorder (ADHD) in children 6 years of age and older and adults up to 65 years of age. Methylphenidate HCl Extended-Release Tablets may help increase attention and decrease impulsiveness and hyperactivity in people with ADHD.

Methylphenidate HCl Extended-Release Tablets are not recommended for use in children under 6 years of age with ADHD.

Methylphenidate HCl Extended-Release Tablets have not been studied in adults older than 65 years of age.

Methylphenidate HCl Extended-Release Tablets are a federally controlled substance (CII) because it contains methylphenidate that can be a target for people who abuse prescription medicines or street drugs. Keep Methylphenidate HCl Extended-Release Tablets in a safe place to protect it from theft. Never give your Methylphenidate HCl Extended-Release Tablets to anyone else because it may cause death or harm them. Selling or giving away Methylphenidate HCl Extended-Release Tablets may harm others and is against the law.

Do not take Methylphenidate HCl Extended-Release Tablets if you or your child:

- are allergic to methylphenidate or any of the ingredients in Methylphenidate HCl Extended-Release Tablets. See the end of this Medication Guide for a complete list of ingredients in Methylphenidate HCl Extended-Release Tablets.
- are taking, or have stopped taking within the past 14 days, a medicine called monoamine oxidase inhibitor (MAOI)

Before taking Methylphenidate HCl Extended-Release Tablets, tell your healthcare provider about all of your or your child’s medical conditions, including if you or your child:

- have heart problems, heart disease, heart defects, or high blood pressure
- have mental problems including psychosis, mania, bipolar illness, or depression, or have a family history of suicide, bipolar illness, or depression
- have or have had seizures or have had an abnormal brain wave test (EEG)
- have circulation problems in fingers and toes
- have had a blockage or narrowing of the intestines
- have eye problems, including increased pressure in your eye, glaucoma, or problems with your close-up vision (farsightedness)
- have or had repeated movements or sounds (tics) or Tourette’s syndrome, or have a family history of tics or Tourette’s syndrome
- are pregnant or plan to become pregnant. It is not known if Methylphenidate HCl Extended-Release Tablets will harm the unborn baby.
- are breastfeeding or plan to breastfeed. It is not known if Methylphenidate HCl Extended-Release passes into the breastmilk. Talk to your healthcare provider about the best way to feed the baby during treatment with Methylphenidate HCl Extended-Release Tablets.

Tell your healthcare provider about all of the medicines that you or your child take, including prescription and over-the-counter medicines, vitamins, and herbal supplements.

Methylphenidate HCl Extended-Release Tablets and some medicines may interact with each other and cause serious side effects. Sometimes the doses of other medicines will need to be changed during treatment with Methylphenidate HCl Extended-Release Tablets. Your healthcare provider will decide whether Methylphenidate HCl Extended-Release Tablets can be taken with other medicines.

Especially tell your healthcare provider if you or your child take:

- a medicine to treat blood pressure
- coumarin anticoagulants (a medicine that prevent blood clots, such as warfarin)
- a medicine to treat seizures
- a medicine to treat depression
- risperidone

Know the medicines that you or your child take. Keep a list of your or your child’s medicines with you to show your healthcare provider and pharmacist when you or your child get a new medicine.

Do not start any new medicine during treatment with Methylphenidate HCl Extended-Release Tablets without first talking to your healthcare provider.

How should Methylphenidate HCl Extended-Release Tablets be taken?

- Take Methylphenidate HCl Extended-Release Tablets exactly as prescribed by your or your child’s healthcare provider.
- Your healthcare provider may change the dose or tell you to stop taking Methylphenidate HCl Extended-Release Tablets if needed.
- Take Methylphenidate HCl Extended-Release Tablets 1 time each day in the morning with or without food.
- Swallow Methylphenidate HCl Extended-Release Tablets whole with water or other liquids. Do not chew, crush, or divide the tablets. Tell your healthcare provider if you or your child cannot swallow Methylphenidate HCl Extended-Release Tablets whole. A different medicine may need to be prescribed.
- Methylphenidate HCl Extended-Release Tablets do not dissolve completely in the body after all the medicine has been released. You or your child may sometimes notice the empty tablet in a bowel movement. This is normal.
- Your healthcare provider may do blood tests during treatment with Methylphenidate HCl Extended-Release Tablets to check your or your child’s blood count.

If you or your child take too much Methylphenidate HCl Extended-Release Tablets, call your healthcare provider or Poison Help line at 1-800-222-1222 or go to the nearest hospital emergency room right away.

What are the possible side effects of Methylphenidate HCl Extended-Release Tablets?

Methylphenidate HCl Extended-Release Tablets may cause serious side effects, including:

- See “What is the most important information I should know about Methylphenidate HCl Extended-Release Tablets?”
- Seizures. Your healthcare provider will stop treatment with Methylphenidate HCl Extended-Release Tablets if you or your child have a seizure.
- Painful and prolonged erections (priapism). Priapism that may require surgery has happened in people who take products that contain methylphenidate. If you or your child develop priapism, get medical help right away.
- Circulation problems in fingers and toes (peripheral vasculopathy, including Raynaud’s phenomenon).

Signs and symptoms may include:

- fingers or toes may feel numb, cool, painful
- fingers or toes may change color from pale, to blue, to red

Tell your healthcare provider if you or your child have any numbness, pain, skin color change, or sensitivity to temperature in your fingers or toes.

Call your healthcare provider right away if you or your child have any signs of unexplained wounds appearing on fingers or toes during treatment with Methylphenidate HCl Extended-Release Tablets.

- Slowing of growth (height and weight) in children. Children should have their height and weight checked often during treatment with Methylphenidate HCl Extended-Release Tablets. Methylphenidate HCl Extended-Release Tablets treatment may be stopped if your child is not growing or gaining weight as expected.
- Eye problems (increased pressure in the eye and glaucoma). Call your healthcare provider right away if you or your child develop changes in your vision or eye pain, swelling, or redness.
- New or worsening tics or worsening Tourette’s syndrome. Tell your healthcare provider if you or your child get any new or worsening tics or worsening Tourette’s syndrome during treatment with Methylphenidate HCl Extended-Release Tablets.
- Eyesight changes or blurred vision.
- Possible blockage of the intestine. Because the Methylphenidate HCl Extended-Release Tablet does not change in shape in the intestines (GI tract), Methylphenidate HCl Extended-Release Tablets should not be taken by people with severe intestinal problems (preexisting severe gastrointestinal narrowing).

The most common side effect of Methylphenidate HCl Extended-Release Tablets in children is upper stomach-area (abdominal) pain.

The most common side effects of Methylphenidate HCl Extended-Release Tablets in adults include:

- decreased appetite
- headache
- dry mouth
- nausea
- trouble sleeping
- anxiety
- dizziness
- weight loss
- irritability
- increased sweating

These are not all the possible side effects of Methylphenidate HCl Extended-Release Tablets.

Call your doctor for medical advice about side effects. You may report side effects to FDA at 1-800-FDA-1088.

You may also report side effects to Kremers Urban Pharmaceuticals Inc. at 1-844-834-0530.

How should I store Methylphenidate HCl Extended-Release Tablets?

- Store Methylphenidate HCl Extended-Release Tablets at room temperature between 59°F to 86°F (15°C to 30°C).
- Protect from moisture.
- Store Methylphenidate HCl Extended-Release Tablets in a safe place, like a locked cabinet.
- Dispose of remaining, unused, or expired Methylphenidate HCl Extended-Release Tablets by a medicine take-back program at a U.S. Drug Enforcement Administration (DEA) authorized collection site. If no take-back program or DEA authorized collector is available, mix Methylphenidate HCl Extended-Release Tablets with an undesirable, nontoxic substance such as dirt, cat litter, or used coffee grounds to make it less appealing to children and pets. Place the mixture in a container such as a sealed plastic bag and throw away Methylphenidate HCl Extended-Release Tablets in the household trash. Visit www.fda.gov/drugdisposal for additional information on disposal of unused medicines.

Keep Methylphenidate HCl Extended-Release Tablets and all medicines out of the reach of children.

General information about the safe and effective use of Methylphenidate HCl Extended-Release Tablets.

Medicines are sometimes prescribed for purposes other than those listed in a Medication Guide. Do not use Methylphenidate HCl Extended-Release Tablets for a condition for which it was not prescribed. Do not give Methylphenidate HCl Extended-Release Tablets to other people, even if they have the same condition. It may harm them and it is against the law.

You can ask your healthcare provider or pharmacist for information about Methylphenidate HCl Extended-Release Tablets that is written for healthcare professionals.

What are the ingredients in Methylphenidate HCl Extended-Release Tablets?

Active ingredient: methylphenidate hydrochloride

Inactive ingredients: carboxymethylcellulose sodium, colloidal silicon dioxide, corn starch, ethocel, hydroxypropyl cellulose, hypromellose, hypromellose acetate succinate, magnesium stearate, microcrystalline cellulose, polyethylene glycol, sucrose, talc, titanium dioxide and triethyl citrate. The 18, 36, and 54 mg tablets also contain synthetic red iron oxide. The 27 mg tablets also contain yellow iron oxide.

Manufactured by:

Kremers Urban Pharmaceuticals Inc.

Seymour, IN 47274

For more information call 1-844-834-0530.

CIA75798L

Rev. 01/2026

This Medication Guide has been approved by the U.S. Food and Drug Administration.

18 mg 100 Count Bottle Label

PRINCIPAL DISPLAY PANEL

NDC 62175-310-37

Methylphenidate HCl
Extended-Release Tablets, USP

18 mg

PHARMACIST: Dispense the
accompanying Medication Guide
to each patient.

Print Medication Guides at www.lannett.com/

med-guide/methylphenidate-er-tabs-bx

Rx Only

100 Tablets

27 mg 100 Count Bottle Label

PRINCIPAL DISPLAY PANEL

NDC 62175-311-37

Methylphenidate HCl
Extended-Release Tablets, USP

27 mg

PHARMACIST: Dispense the
accompanying Medication Guide
to each patient.

Print Medication Guides at www.lannett.com/

med-guide/methylphenidate-er-tabs-bx

Rx Only

100 Tablets

36 mg 100 Count Bottle Label

PRINCIPAL DISPLAY PANEL

NDC 62175-311-37

Methylphenidate HCl
Extended-Release Tablets, USP

36 mg

PHARMACIST: Dispense the
accompanying Medication Guide
to each patient.

Print Medication Guides at www.lannett.com/

med-guide/methylphenidate-er-tabs-bx

Rx Only

100 Tablets

54 mg 100 Count Bottle Label

PRINCIPAL DISPLAY PANEL

NDC 62175-313-37

Methylphenidate HCl
Extended-Release Tablets, USP

54 mg

Rx Only

PHARMACIST: Dispense the
accompanying Medication Guide
to each patient.

Print Medication Guides at www.lannett.com/

med-guide/methylphenidate-er-tabs-bx

Rx Only

100 Tablets